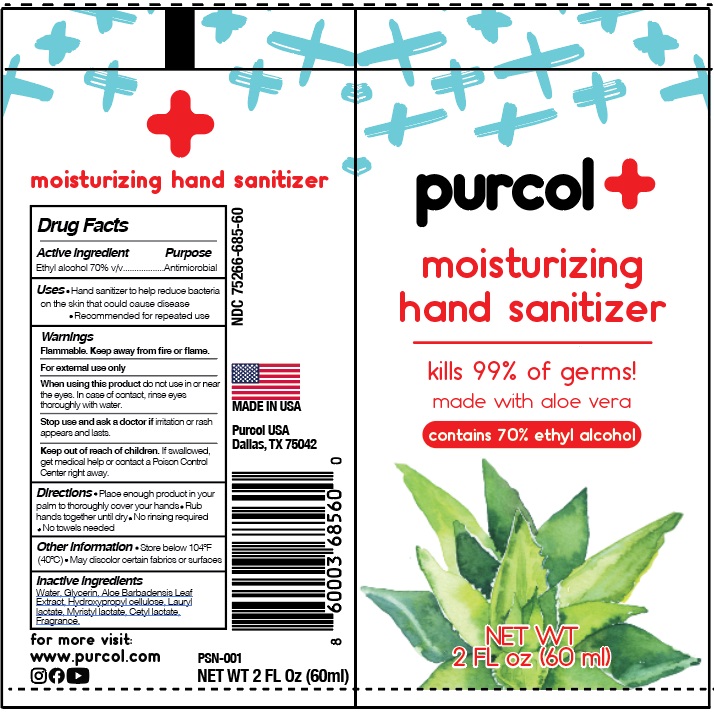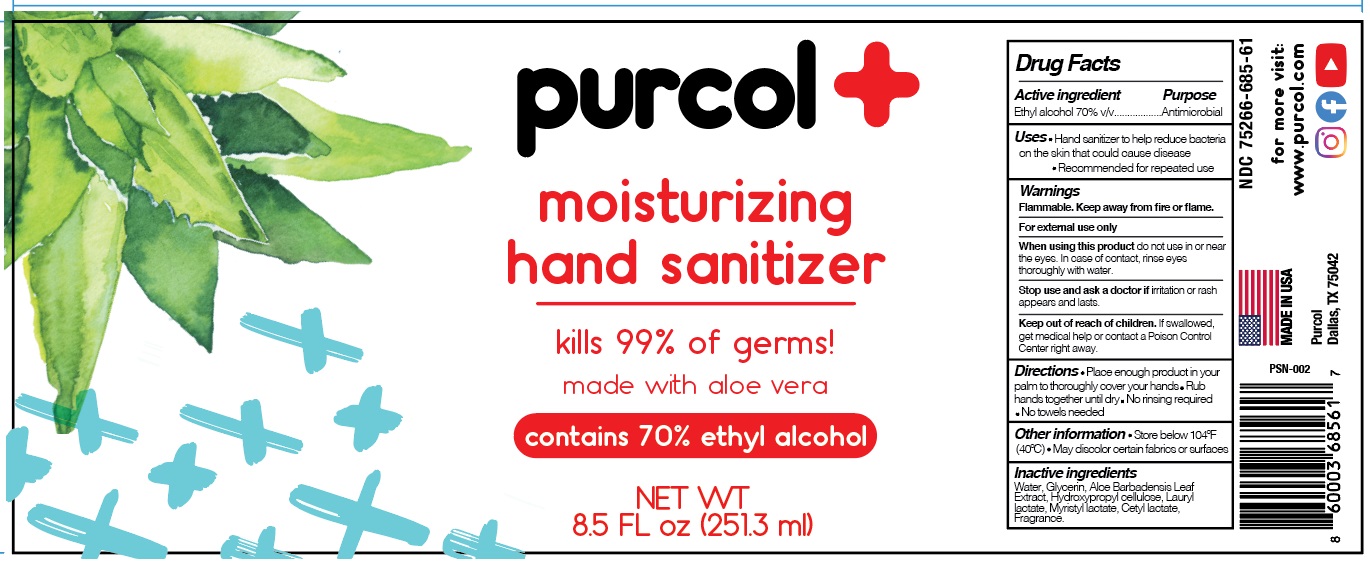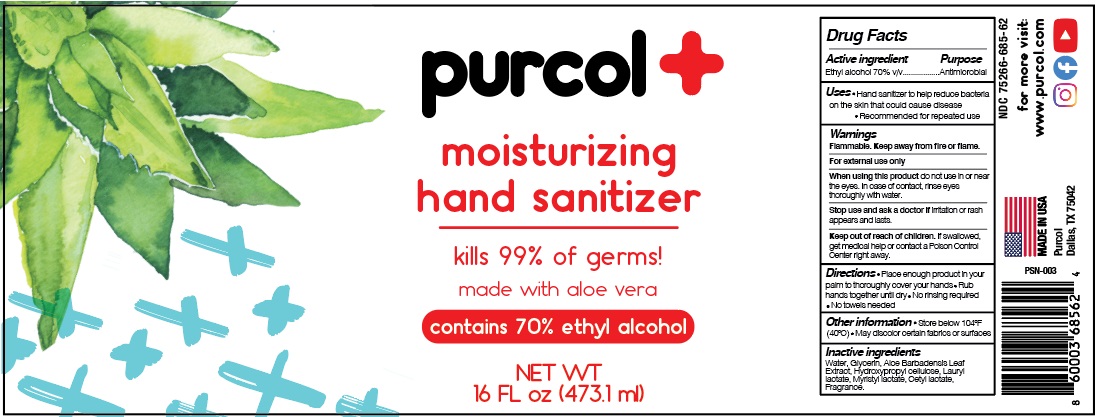 DRUG LABEL: Purcol Moisturizing Hand Sanitizer
NDC: 75266-685 | Form: GEL
Manufacturer: Purocol LLC
Category: otc | Type: HUMAN OTC DRUG LABEL
Date: 20220301

ACTIVE INGREDIENTS: ALCOHOL 0.7 mL/1 mL
INACTIVE INGREDIENTS: WATER; GLYCERIN; ALOE VERA LEAF; HYDROXYPROPYL CELLULOSE, UNSPECIFIED; LAURYL LACTATE; MYRISTYL LACTATE; CETYL LACTATE

Purcol Moisturizing Hand Sanitizer

Active Ingredient

Ethyl alcohol 70% v/v

Purpose

Antimicrobial

Uses

- Hand sanitizer to help reduce bacteria on the skin that could cause disease
- Recommended for repeated use

Warnings

Flammable. Keep away from fire or flame.

For external use only

When using this product

do not use in or near the eyes. In case of contact, rinse eyes thoroughly with water.

Stop use and ask a doctor if

irritation or rash appears and lasts.

Keep out of reach of children.

If swallowed, get medical help or contact a Poison Control Center right away.

Directions

- Place enough product in your palm to thoroughly cover your hands
- Rub hands together until dry
- No rinsing required
- No towels needed

Other Information

- Store below 104°F (40°C)
- May discolor certain fabrics or surfaces

Inactive Ingredients

Water, Glycerin, Aloe Barbadensis Leaf Extract, Hydroxypropyl cellulose, Lauryl lactate, Myristyl lactate, Cetyl lactate, Fragrance.